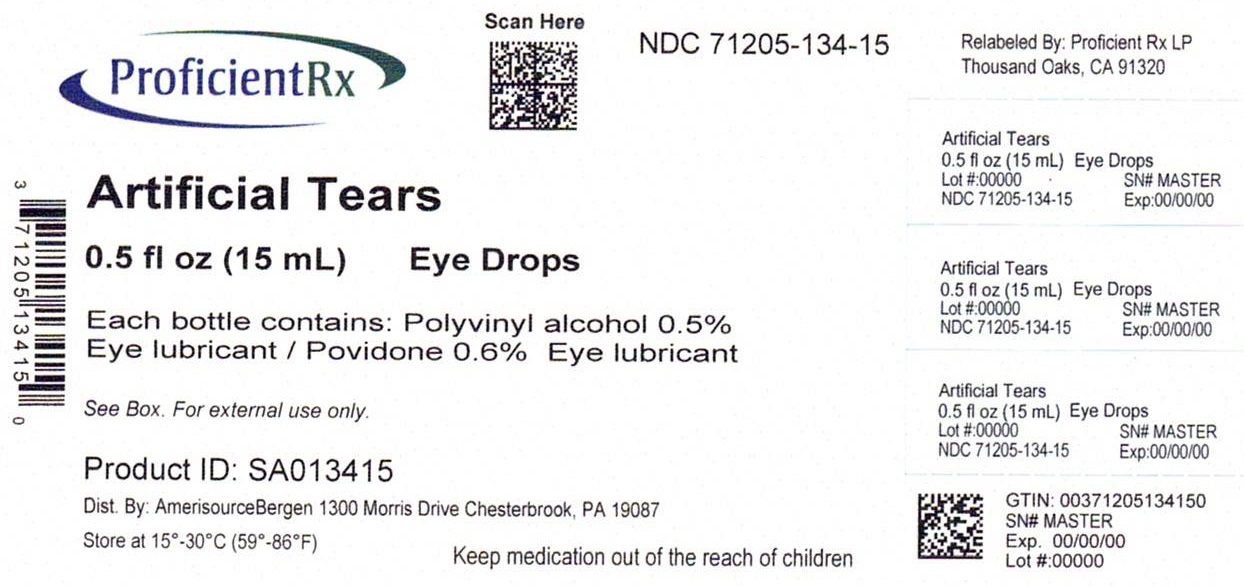 DRUG LABEL: Good Neighbor Pharmacy Artifical Tears Lubricant Eye Drops
NDC: 71205-134 | Form: SOLUTION/ DROPS
Manufacturer: Proficient Rx LP
Category: otc | Type: HUMAN OTC DRUG LABEL
Date: 20231201

ACTIVE INGREDIENTS: POLYVINYL ALCOHOL, UNSPECIFIED .5 g/100 mL; POVIDONE, UNSPECIFIED .6 g/100 mL
INACTIVE INGREDIENTS: BENZALKONIUM CHLORIDE; DEXTROSE, UNSPECIFIED FORM; EDETATE DISODIUM; POTASSIUM CHLORATE; WATER; SODIUM BICARBONATE; SODIUM CHLORIDE; SODIUM CITRATE, UNSPECIFIED FORM; SODIUM PHOSPHATE, DIBASIC, UNSPECIFIED FORM; SODIUM PHOSPHATE, MONOBASIC, UNSPECIFIED FORM

Good Neighbor Pharmacy Artifical Tears Lubricant Eye Drops

Active ingredients

Polyvinyl alcohol 0.5%

Povidone 0.6%

Purpose

Eye lubricant

Uses

- for use as a protectant against further irritation or to relieve dryness of the eye
- for the temporary relief of discomfort due to minor irritations of the eye, or to exposure to wind or sun

Warnings

For external use only

Do not use this product if

solution changes color or becomes cloudy

Stop use and ask a doctor if you experience

to avoid contamination, do not touch tip of container to any surface
replace cap after using. Keep container tightly closed.
remove contact lens before using

Keep out of the reach of children.

If accidentally swallowed, get medical help or contact a Poison Control Center immediately.

Directions

Instill 1 or 2 drops in the affected eye(s) as needed.

Other information

Tamper Evident. Do not use this product if imprinted neckband is missing or broken.
RETAIN THISCARTON FOR FUTURE REFERENCE
Store at 15°-30°C (59°-86°F)

Inactive ingredients

benzalkonium chloride, dextrose, edetate disodium, potassium chloride, purified water, sodium bicarbonate, sodium chloride, sodium citrate, sodium phosphate dibasic, and sodium phosphate monobasic

This product is not

manufactured or distributed

by Prestige Brands International,

Inc., distributor of Murine®

Tears

TM

*

Artificial

Lubcricant Eye Drops

Tears

STERILE

Magenta

Yellow Cyan

Questions? Call 1-888-527-4276

Relabeled by:

Proficient Rx LP

Thousand Oaks, CA 91320